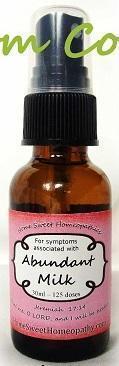 DRUG LABEL: Abundant Milk
NDC: 59667-0001 | Form: SPRAY
Manufacturer: Home Sweet Homeopathics
Category: homeopathic | Type: HUMAN OTC DRUG LABEL
Date: 20130801

ACTIVE INGREDIENTS: ACONITUM NAPELLUS 30 [hp_C]/30 [hp_C]; CHASTE TREE 30 [hp_C]/30 [hp_C]; ALFALFA 30 [hp_C]/30 [hp_C]; ASAFETIDA 30 [hp_C]/30 [hp_C]; OYSTER SHELL CALCIUM CARBONATE, CRUDE 30 [hp_C]/30 [hp_C]; MATRICARIA RECUTITA 30 [hp_C]/30 [hp_C]; CAUSTICUM 30 [hp_C]/30 [hp_C]; SOLANUM DULCAMARA TOP 30 [hp_C]/30 [hp_C]; CANIS LUPUS FAMILIARIS MILK 30 [hp_C]/30 [hp_C]; LACTUCA VIROSA 30 [hp_C]/30 [hp_C]; PHOSPHORIC ACID 30 [hp_C]/30 [hp_C]; PULSATILLA VULGARIS 30 [hp_C]/30 [hp_C]; RICINUS COMMUNIS WHOLE 30 [hp_C]/30 [hp_C]; TOXICODENDRON PUBESCENS LEAF 30 [hp_C]/30 [hp_C]; SILICON DIOXIDE 30 [hp_C]/30 [hp_C]; SULFUR 30 [hp_C]/30 [hp_C]; THYROID, UNSPECIFIED 30 [hp_C]/30 [hp_C]; URTICA URENS 30 [hp_C]/30 [hp_C]; ZINC 30 [hp_C]/30 [hp_C]
INACTIVE INGREDIENTS: WATER; ALCOHOL

PURPOSE

To help increase milk supply.

To be used according to label indications.

Active Ingredients:

Aconite 30c,

Agnus Castus 30c,

Alfalfa 30c,

Asafeotida 30c,

Calcarea Carb 30c,

Chamomilla 30c,

Causticum 30c,

Dulcamara 30c,

Lac Caninum 30c,

Lactuca Virosa 30c,

Phosphoricum A. 30c,

Pulsatilla 30c,

Ricinus 30c,

Rhus Tox 30c,

Silicea 30c,

Sulphur 30c

Thyroidinum 30c,

Urtica Urens 30c,

Zinc 30c

Directions:

Spritz 1 time under the tongue 3 x per day until improvement is seen, then dose 1x per day for 3 days. Dose when symptoms return.

Keep out of reach of children.

WARNINGS

If no improvement is seen after 7 days or new symptoms develop, discontinue use.

Inactive Ingredients:

In reverse osmosis water with less than 1% alcohol. May contain trace amounts of lactose.